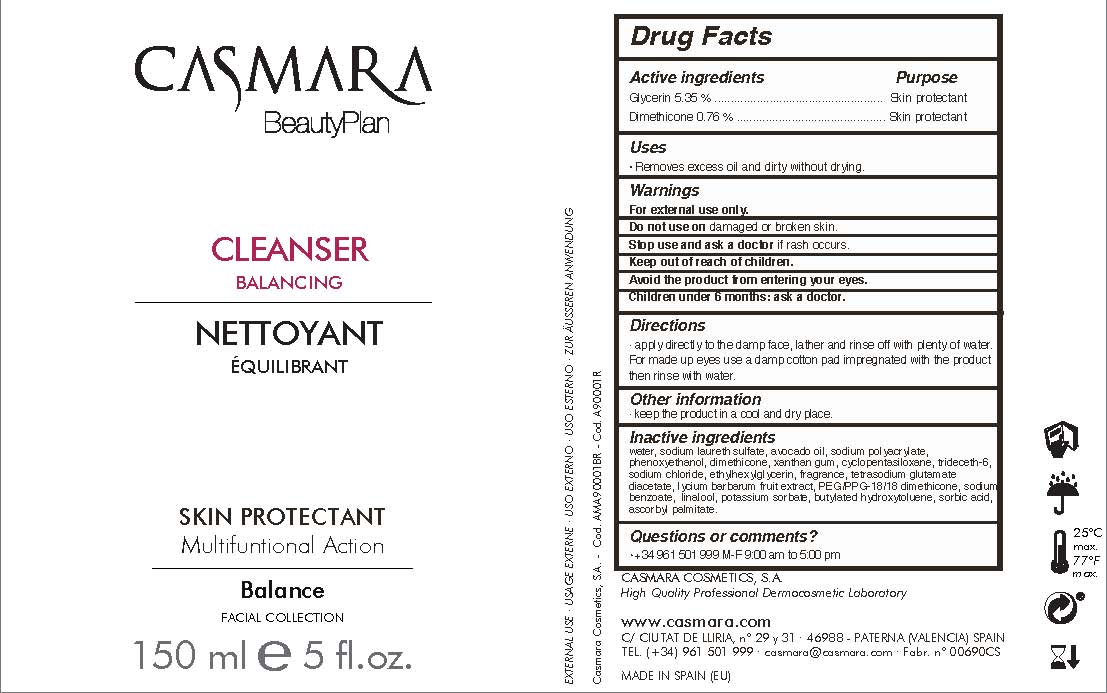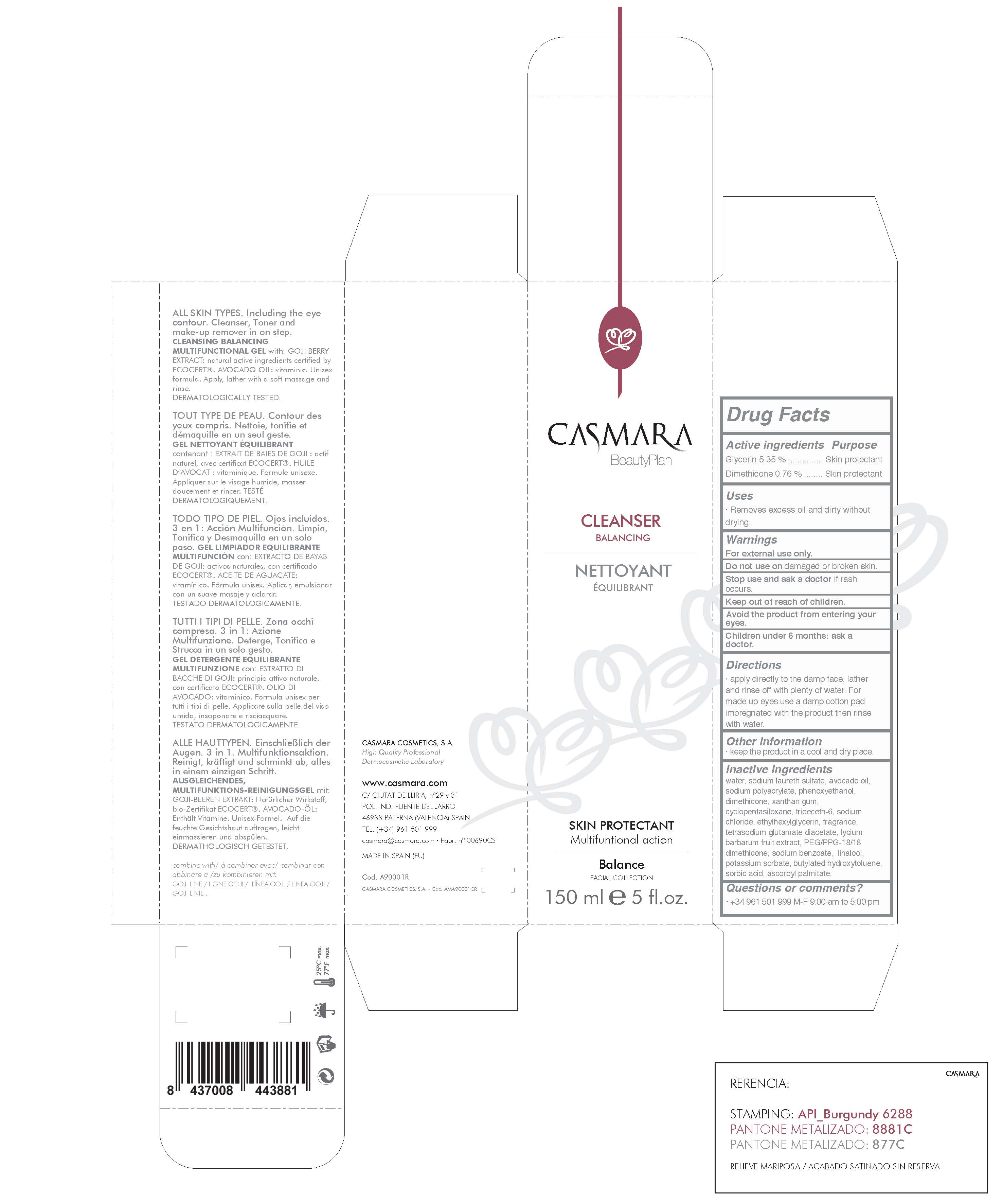 DRUG LABEL: Cleanser Balancing
NDC: 20151-069 | Form: LIQUID
Manufacturer: Casmara Cosmetics, SA
Category: otc | Type: HUMAN OTC DRUG LABEL
Date: 20161101

ACTIVE INGREDIENTS: DIMETHICONE 0.76 mg/1 mL; GLYCERIN 5.35 mg/1 mL
INACTIVE INGREDIENTS: ASCORBYL PALMITATE 0.0006 mg/1 mL; BUTYLATED HYDROXYTOLUENE 0.01 mg/1 mL; SORBIC ACID 0.002 mg/1 mL; POTASSIUM SORBATE 0.01 mg/1 mL; SODIUM LAURETH SULFATE 2.7 mg/1 mL; AVOCADO OIL 1.5 mg/1 mL; ETHYLHEXYLGLYCERIN 0.1 mg/1 mL; WATER 86.02 mg/1 mL; PHENOXYETHANOL 0.9 mg/1 mL; TETRASODIUM GLUTAMATE DIACETATE 0.094 mg/1 mL; SODIUM POLYACRYLATE (8000 MW) 1.04 mg/1 mL; PERFLUNAFENE 0.1 mg/1 mL; XANTHAN GUM 0.5 mg/1 mL; CYCLOMETHICONE 5 0.36 mg/1 mL; TRIDECETH-6 0.24 mg/1 mL; SODIUM CHLORIDE 0.16 mg/1 mL; LYCIUM BARBARUM FRUIT 0.06 mg/1 mL; PEG/PPG-18/18 DIMETHICONE 0.04 mg/1 mL; SODIUM BENZOATE 0.035 mg/1 mL; LINALOOL, (+)- 0.01003 mg/1 mL

Cleanser Balancing Skin Protectant Multifuntional Action

Active Ingredients

Glycerin 5,35%........................... Skin Protectant

Dimethicone 0,76%.....................Skin Protectant

WARNINGS

For external use only.

Do not use on damaged or broken skin.

Stop use and ask a doctor if rash occurs.

Keep out of reach of children.

Avoid the product from entering your eyes.

Children under 6 months: as a doctor.

Stop use and ask a doctor if rash occurs

Children under 6 months: ask a doctor

. keep out of reach of children

Questions or comments? + 34 961 501 099 M-F 9:00 am to 5:00 pm

OTHER SAFETY INFORMATION

. keep the product in a cool and dry place

Directions

. apply directly to the damp face, lather and rinse off with plenty of water.

. for made up eyes use a damp cotton pad impregnated with the product, then rinse with water

DOSAGE AND ADMINISTRATION

. apply directly to the damp face, lather and rinse off with plenty of water.

. for made up eyes use a damp cotton pad impregnated with the product, then rinse with water

Uses

. removes excess oil and dirty without drying

INACTIVE INGREDIENT

water, sodium laureth sulfate, avocado oil, sodium polyacrylate, phenoxyethanol, xanthan gum, cyclopentasiloxane, trideceth-6, sodium chloride, ethylhexylglycerin, fragrance, tetrasodium glutamate diacetate, lycium barbarum fruit extract, PEG/PPG-18/18 dimethicone, sodium benzoate, linalool, postasium sorbate, butylated hydroxytoluene, sorbic acid, ascorbyl palmitate.

PURPOSE

. removes excess oil and dirty without drying.

PACKAGE LABEL

Cleanser Balancing

Skin protectant

Multifuntional action

Balance

Facial Collection